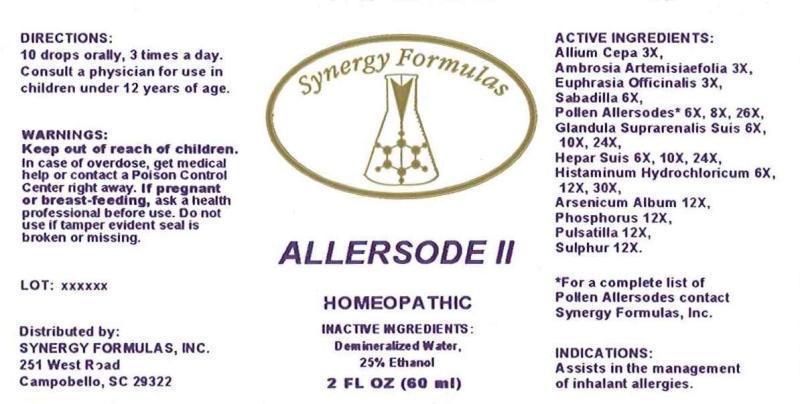 DRUG LABEL: ALLERSODE
NDC: 43772-0014 | Form: LIQUID
Manufacturer: Synergy Formulas, Inc.
Category: homeopathic | Type: HUMAN OTC DRUG LABEL
Date: 20150421

ACTIVE INGREDIENTS: ONION 3 [hp_X]/1 mL; AMBROSIA ARTEMISIIFOLIA 6 [hp_X]/1 mL; EUPHRASIA STRICTA 3 [hp_X]/1 mL; SCHOENOCAULON OFFICINALE SEED 6 [hp_X]/1 mL; RUMEX ACETOSELLA POLLEN 6 [hp_X]/1 mL; RUMEX CRISPUS TOP 6 [hp_X]/1 mL; POA PRATENSIS TOP 6 [hp_X]/1 mL; DACTYLIS GLOMERATA TOP 6 [hp_X]/1 mL; AGROSTIS GIGANTEA POLLEN 6 [hp_X]/1 mL; PHLEUM PRATENSE TOP 6 [hp_X]/1 mL; SOLIDAGO VIRGAUREA FLOWERING TOP 6 [hp_X]/1 mL; TRIFOLIUM PRATENSE FLOWER 6 [hp_X]/1 mL; ALFALFA 6 [hp_X]/1 mL; AMBROSIA TRIFIDA POLLEN 6 [hp_X]/1 mL; AMBROSIA ACANTHICARPA POLLEN 6 [hp_X]/1 mL; AMBROSIA PSILOSTACHYA POLLEN 6 [hp_X]/1 mL; ULMUS AMERICANA POLLEN 6 [hp_X]/1 mL; PLATANUS OCCIDENTALIS POLLEN 6 [hp_X]/1 mL; FRAXINUS AMERICANA POLLEN 6 [hp_X]/1 mL; FAGUS GRANDIFOLIA POLLEN 6 [hp_X]/1 mL; JUGLANS NIGRA POLLEN 6 [hp_X]/1 mL; SALIX NIGRA POLLEN 6 [hp_X]/1 mL; ACER NEGUNDO POLLEN 6 [hp_X]/1 mL; POPULUS DELTOIDES SUBSP. DELTOIDES POLLEN 6 [hp_X]/1 mL; BETULA OCCIDENTALIS POLLEN 6 [hp_X]/1 mL; QUERCUS RUBRA POLLEN 6 [hp_X]/1 mL; CARYA OVATA POLLEN 6 [hp_X]/1 mL; SUS SCROFA ADRENAL GLAND 6 [hp_X]/1 mL; PORK LIVER 6 [hp_X]/1 mL; HISTAMINE DIHYDROCHLORIDE 6 [hp_X]/1 mL; ARSENIC TRIOXIDE 12 [hp_X]/1 mL; PHOSPHORUS 12 [hp_X]/1 mL; PULSATILLA VULGARIS 12 [hp_X]/1 mL; SULFUR 12 [hp_X]/1 mL
INACTIVE INGREDIENTS: WATER; ALCOHOL

DRUG FACTS:

ACTIVE INGREDIENTS:

Allium Cepa 3X, Ambrosia Artemisiaefolia 3X, Euphrasia Officinalis 3X, Sabadilla 6X, Alfalfa 6X, 8X, 26X, American Elm 6X, 8X, 26X, American Sycamore 6X, 8X, 26X, Ash 6X, 8X, 26X, American Beech 6X, 8X, 26X, Black Walnut 6X, 8X, 26X, Black Willow 6X, 8X, 26X, Box Elder 6X, 8X, 26X, Eastern Cottonwood 6X, 8X, 26X, False Ragweed 6X, 8X, 26X, Giant Ragweed 6X, 8X, 26X, Goldenrod 6X, 8X, 26X, Kentucky Bluegrass 6X, 8X, 26X, Orchard Grass 6X, 8X, 26X, Red Birch 6X, 8X, 26X, Red Clover 6X, 8X, 26X, Red Oak 6X, 8X, 26X, Redtop Grass 6X, 8X, 26X, Hickory 6X, 8X, 26X, Sheep Sorrel 6X, 8X, 26X, Short Ragweed 6X, 8X, 26X, Timothy Grass 6X, 8X, 26X, Western Ragweed 6X, 8X, 26X, Yellow Dock 6X, 8X, 26X, Glandula Suprarenalis Suis 6X, 10X, 24X, Hepar Suis 6X, 10X, 24X, Histaminum Hydrochloricum 6X, 12X, 30X, Arsenicum Album 12X, Phosphorus 12X, Pulsatilla (Vulgaris) 12X, Sulphur 12X.

INDICATIONS:

Assists in the management of inhalant allergies.

WARNINGS:

Keep out of reach of children. In case of overdose, get medical help or contact a Poison Control Center right away.

If pregnant or breast-feeding, ask a health professional before use.

Do not use if tamper evident seal is broken or missing.

DIRECTIONS:

10 drops orally, 3 times a day. Consult a physician for use in children under 12 years of age.

INACTIVE INGREDIENTS:

Demineralized Water, 25% Ethanol

Keep out of reach of children. In case of overdose, get medical help or contact a Poison Control Center right away.

INDICATIONS:

Assists in the management of inhalant allergies.

QUESTIONS:

Distributed by:

SYNERGY FORMULAS, INC.

251 West Road

Campobello, SC 29322

*For a complete list of Pollen Allersodes contact Synergy Formulas, Inc.

PACKAGE DISPLAY LABEL:

Synergy Formulas

ALLERSODE II

HOMEOPATHIC

2 FL OZ. (60 mL)